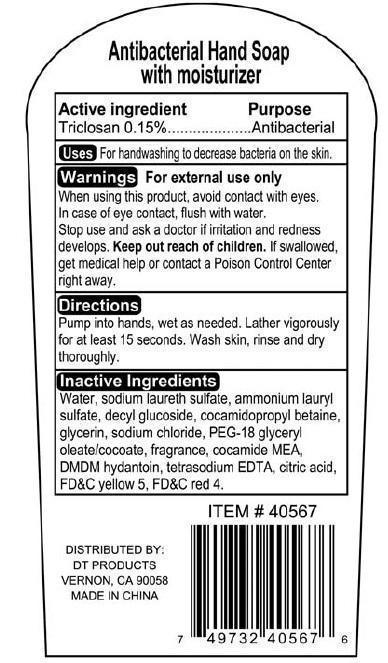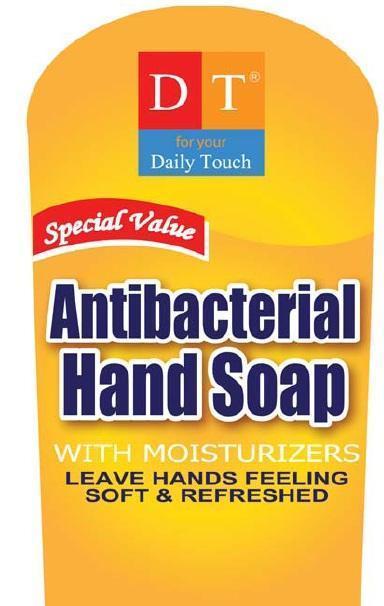 DRUG LABEL: DT ANTIBACTERIAL HAND
NDC: 50523-567 | Form: SOAP
Manufacturer: VOLUME DISTRIBUTORS
Category: otc | Type: HUMAN OTC DRUG LABEL
Date: 20140804

ACTIVE INGREDIENTS: TRICLOSAN 1.5 mg/1 mL
INACTIVE INGREDIENTS: WATER; SODIUM LAURETH SULFATE; AMMONIUM LAURYL SULFATE; COCAMIDOPROPYL BETAINE; GLYCERIN; SODIUM CHLORIDE; DMDM HYDANTOIN; EDETATE SODIUM; CITRIC ACID MONOHYDRATE

DT ANTIBACTERIAL HAND SOAP

ACTIVE INGREDIENT

Anibacterial Hand soap with moisturizer

ACTIVE INGREDIENT PURPOSE

Triclosan 0.15% Antibacterial

PURPOSE
Antibacterial

USES

For handwashing to decrease bacteria on the skin.

WARNINGS

For external use only

When using this product, avoid contact with eyes.

In case of eye contact, flush with water.

Stop use and ask a doctor if irritation and redness develops

Keep out of reach of children.

If swallowed, get medical help or contact a Poison Control Center right away.

Directions

Pump into hands, wet as needed. Lather vigorously for at least 15 seconds. Wash skin, rinse and dry thoroughly.

INACTIVE INGREDIENT

Water, sodium laureth sulfate, ammonium lauryl sulfate, decyl glucoside, cocamidopropyl betaine, glycerin, sodium chloride, PEG-18 glyceryl oleate/cocoate, fragrance, cocamide MEA, DMDM Hydantoin, tetrasodium EDTA, citric acid, FDandC yellow 5, FDandC red4

DISTRIBUTED BY:

DT PRODUCTS

VERNON, CA 90058

MADE IN CHINA

PACKAGE LABEL

DT

FOR YOUR DAILY TOUCH

SPECIAL VALUE

Antibacterial

Hand Soap

WITH MOISTURIZERS

LEAVE HANDS FEELING SOFT AND REFRESHED.

16.9 FL OZ (500 ML)